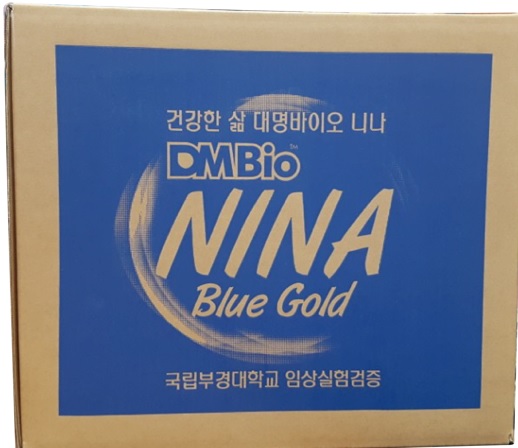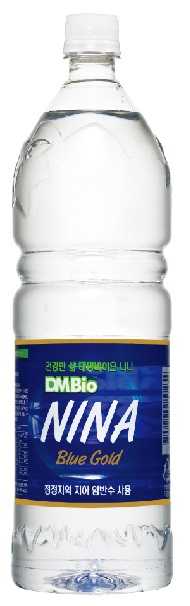 DRUG LABEL: NINA WATER (Rich anions)
NDC: 77008-8112 | Form: LIQUID
Manufacturer: BIOHERB Co., Ltd.
Category: otc | Type: HUMAN OTC DRUG LABEL
Date: 20260101

ACTIVE INGREDIENTS: OXYGEN 0.0029 g/100 g
INACTIVE INGREDIENTS: WATER 99.99 g/100 g

NINA WATER (Rich anions)

INDICATIONS AND USAGE

Mixed drink

KEEP OUT OF THE REACH OF CHILDREN.

DOSAGE AND ADMINISTRATION

Water 99.9971%, Oxygen 0.0029% (29mg/L, When filling up with water)

WARNINGS

● Room Temperature, Shelf-Stable: Best stored at controlled room temperature 20℃ to
25℃ (68℉ to 77℉). Refrigeration in not required, but highly recommended(After
opening the bottle). Extended exposure to direct sunlight, high heat & humidity may
cause product degradation over time. Potency guaranteed until expiration date
when stored in a cool, dry place at 77F(25C) or below.
● Be careful because you may hurt your hands when opening the cap.
● Do not heat it in the microwave.
● Do not drink if the container or lid is deformed or damaged or the contents are deteriorated.
● Precipitates may occur various raw material ingredients, but drink with confidence.
● This product can be exchanged and compensated based on consumer dispute resolution standards.
● After using it, please separate and discharge the packaging container.
● Report of fraudulent or defective food without national code 1339
● Place of return and exchange: 1588-1247 nationwide agencies and stores

PURPOSE

Water

Inactive ingredients:

Water

Active Ingredients

Oxygen

RECENT MAJOR CHANGES

Newly added product